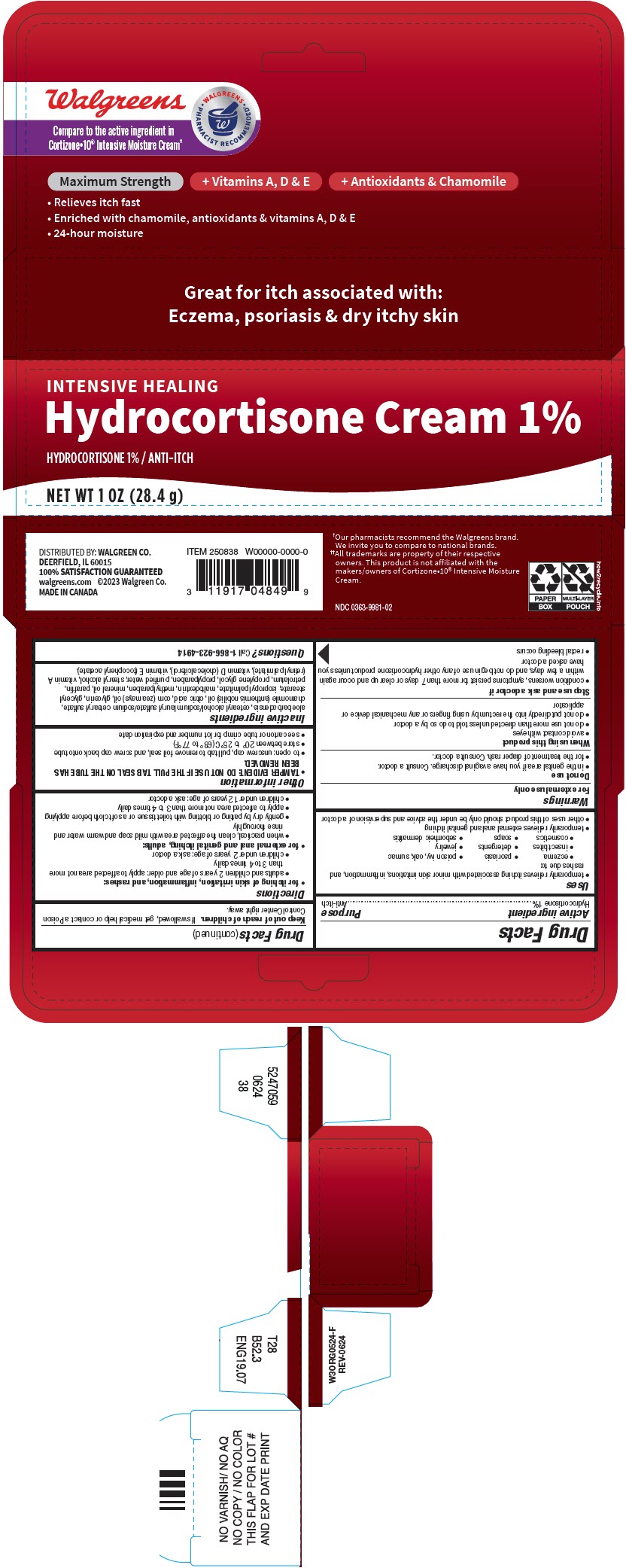 DRUG LABEL: Hydrocortisone
NDC: 0363-9981 | Form: CREAM
Manufacturer: Walgreens Company
Category: otc | Type: HUMAN OTC DRUG LABEL
Date: 20250925

ACTIVE INGREDIENTS: HYDROCORTISONE 10 mg/1 g
INACTIVE INGREDIENTS: ALOE VERA WHOLE; CETOSTEARYL ALCOHOL; SODIUM LAURYL SULFATE; SODIUM CETOSTEARYL SULFATE; CHAMOMILE FLOWER OIL; CITRIC ACID MONOHYDRATE; CORN OIL; GLYCERIN; GLYCERYL MONOSTEARATE; ISOPROPYL PALMITATE; MALTODEXTRIN; METHYLPARABEN; MINERAL OIL; PARAFFIN; PETROLATUM; PROPYLENE GLYCOL; PROPYLPARABEN; WATER; STEARYL ALCOHOL; VITAMIN A PALMITATE; CHOLECALCIFEROL; .ALPHA.-TOCOPHEROL ACETATE

Hydrocortisone Cream

Drug Facts

Active ingredient

Hydrocortisone 1%

Purpose

Anti-itch

Uses

- temporarily relieves itching associated with minor skin irritations, inflammation, and rashes due to:
  - eczema
  - psoriasis
  - poison ivy, oak, sumac
  - insect bites
  - detergents
  - jewelry
  - cosmetics
  - soaps
  - seborrheic dermatitis
- temporarily relieves external anal and genital itching
- other uses of this product should only be under the advice and supervision of a doctor

Warnings

For external use only

Do not use

- in the genital area if you have a vaginal discharge. Consult a doctor.
- for the treatment of diaper rash. Consult a doctor.

When using this product

- avoid contact with eyes
- do not use more than directed unless told to do so by a doctor
- do not put directly into the rectum by using fingers or any mechanical device or applicator

Stop use and ask a doctor if

- condition worsens, symptoms persist for more than 7 days or clear up and occur again within a few days, and do not begin use of any other hydrocortisone product unless you have asked a doctor
- rectal bleeding occurs

Keep out of reach of children.If swallowed, get medical help or contact a Poison Control Center right away.

Directions

- for itching of skin irritation, inflammation, and rashes:
  - adults and children 2 years of age and older: apply to affected area not more than 3 to 4 times daily
  - children under 2 years of age: ask a doctor
- for external anal and genital itching, adults:
  - when practical, clean the affected area with mild soap and warm water and rinse thoroughly
  - gently dry by patting or blotting with toilet tissue or a soft cloth before applying
  - apply to affected area not more than 3 to 4 times daily
  - children under 12 years of age: ask a doctor

Other information

- TAMPER EVIDENT: DO NOT USE IF THE PULL TAB SEAL ON THE TUBE HAS BEEN REMOVED.
- to open: unscrew cap, pull tab to remove foil seal, and screw cap back onto tube
- store between 20° to 25°C (68° to 77°F)
- see carton or tube crimp for lot number and expiration date

Inactive ingredients

aloe barbadensis, cetearyl alcohol/sodium lauryl sulfate/sodium cetearyl sulfate, chamomile (anthemis nobilis) oil, citric acid, corn (zea mays) oil, glycerin, glyceryl stearate, isopropyl palmitate, maltodextrin, methylparaben, mineral oil, paraffin, petrolatum, propylene glycol, propylparaben, purified water, stearyl alcohol, vitamin A (retinyl palmitate), vitamin D (cholecalciferol), vitamin E (tocopheryl acetate).

Questions?

Call 1-866-923-4914

DISTRIBUTED BY: WALGREEN CO.
DEERFIELD, IL 60015

PRINCIPAL DISPLAY PANEL - 28.4 g Tube Carton

INTENSIVE HEALING

Hydrocortisone Cream 1%

HYDROCORTISONE 1% / ANTI-ITCH

NET WT 1 OZ (28.4 g)